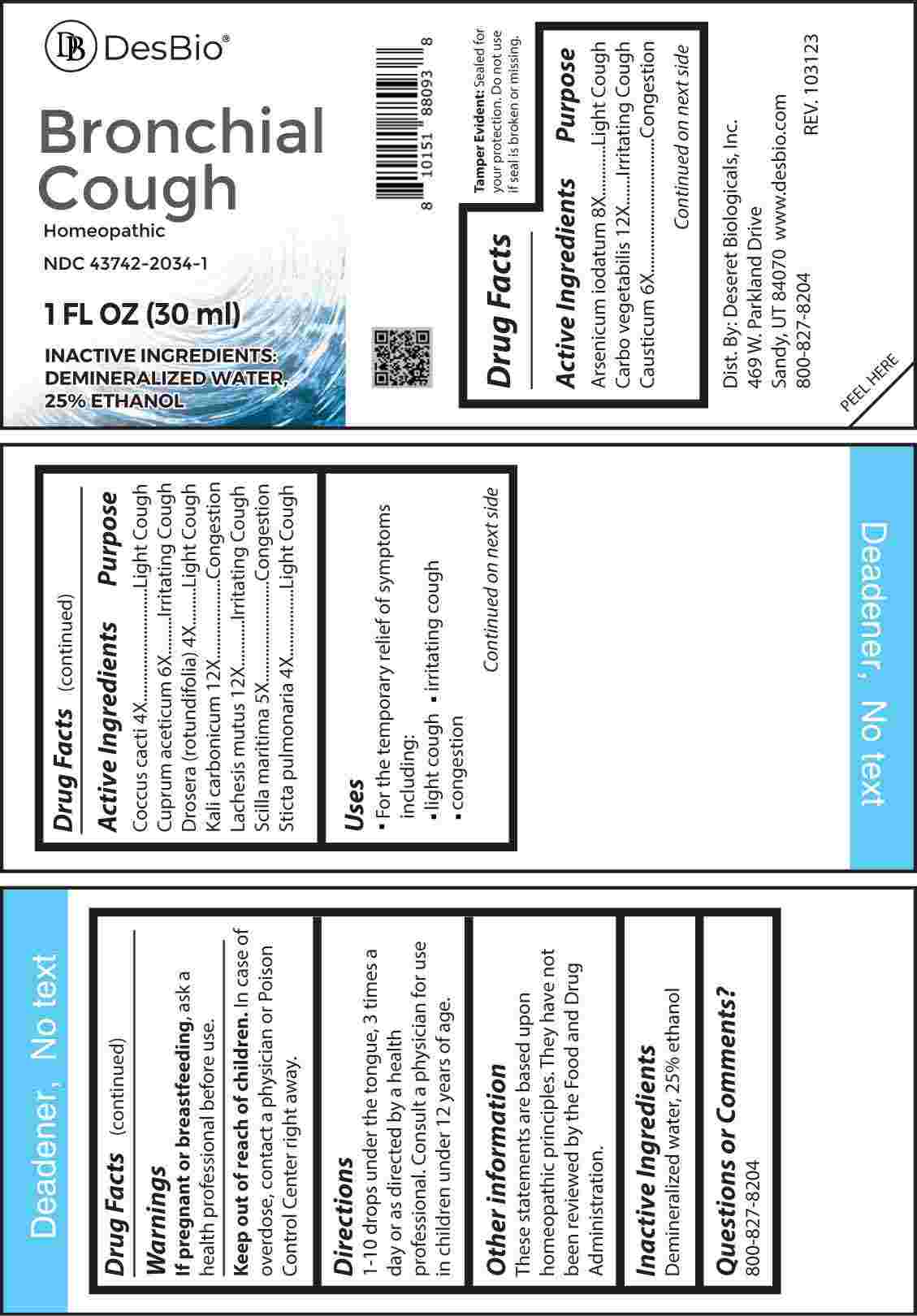 DRUG LABEL: Bronchial Cough
NDC: 43742-2034 | Form: LIQUID
Manufacturer: Deseret Biologicals, Inc.
Category: homeopathic | Type: HUMAN OTC DRUG LABEL
Date: 20240221

ACTIVE INGREDIENTS: PROTORTONIA CACTI 4 [hp_X]/1 mL; DROSERA ROTUNDIFOLIA WHOLE 4 [hp_X]/1 mL; LOBARIA PULMONARIA 4 [hp_X]/1 mL; DRIMIA MARITIMA BULB 5 [hp_X]/1 mL; CAUSTICUM 6 [hp_X]/1 mL; CUPRIC ACETATE 6 [hp_X]/1 mL; ARSENIC TRIIODIDE 8 [hp_X]/1 mL; ACTIVATED CHARCOAL 12 [hp_X]/1 mL; POTASSIUM CARBONATE 12 [hp_X]/1 mL; LACHESIS MUTA VENOM 12 [hp_X]/1 mL
INACTIVE INGREDIENTS: WATER; ALCOHOL

DRUG FACTS:

ACTIVE INGREDIENTS:

Arsenicum Iodatum 8X, Carbo Vegetabilis 12X, Causticum 6X, Coccus Cacti 4X, Cuprum Aceticum 6X, Drosera (Rotundifolia) 4X, Kali Carbonicum 12X, Lachesis Mutus 12X, Scilla Maritima 5X, Sticta Pulmonaria 4X.

PURPOSE:

Arsenicum Iodatum – Light Cough, Carbo Vegetabilis – Irritating Cough, Causticum - Congestion, Coccus Cacti – Light Cough, Cuprum Aceticum – Irritating Cough, Drosera (Rotundifolia) – Light Cough, Kali Carbonicum - Congestion, Lachesis Mutus – Irritating Cough, Scilla Maritima - Congestion, Sticta Pulmonaria – Light Cough

USES:

• For the temporary relief of symptoms including:

• light cough • irritating cough • congestion

These statements are based upon homeopathic principles. They have not been reviewed by the Food and Drug Administration.

WARNINGS:

If pregnant or breast-feeding, ask a health professional before use.

Keep out of reach of children. In case of overdose, contact a physician or Poison Control Center right away.

Tamper Evident: Sealed for your protection. Do not use if seal is broken or missing.

KEEP OUT OF REACH OF CHILDREN:

In case of overdose, contact a physician or Poison Control Center right away.

DIRECTIONS:

1-10 drops under the tongue, 3 times a day or as directed by a health professional. Consult a physician for use in children under 12 years of age.

INACTIVE INGREDIENTS:

Demineralized water, 25% ethanol

QUESTIONS:

Dist. By: Deseret Biologicals, Inc.
469 W. Parkland Drive
Sandy, UT 84070

www.desbio.com

800-827-8204

PACKAGE LABEL DISPLAY:

Des Bio

Bronchial Cough

Homeopathic

NDC 43742-2034-1

1 FL OZ (30 ml)